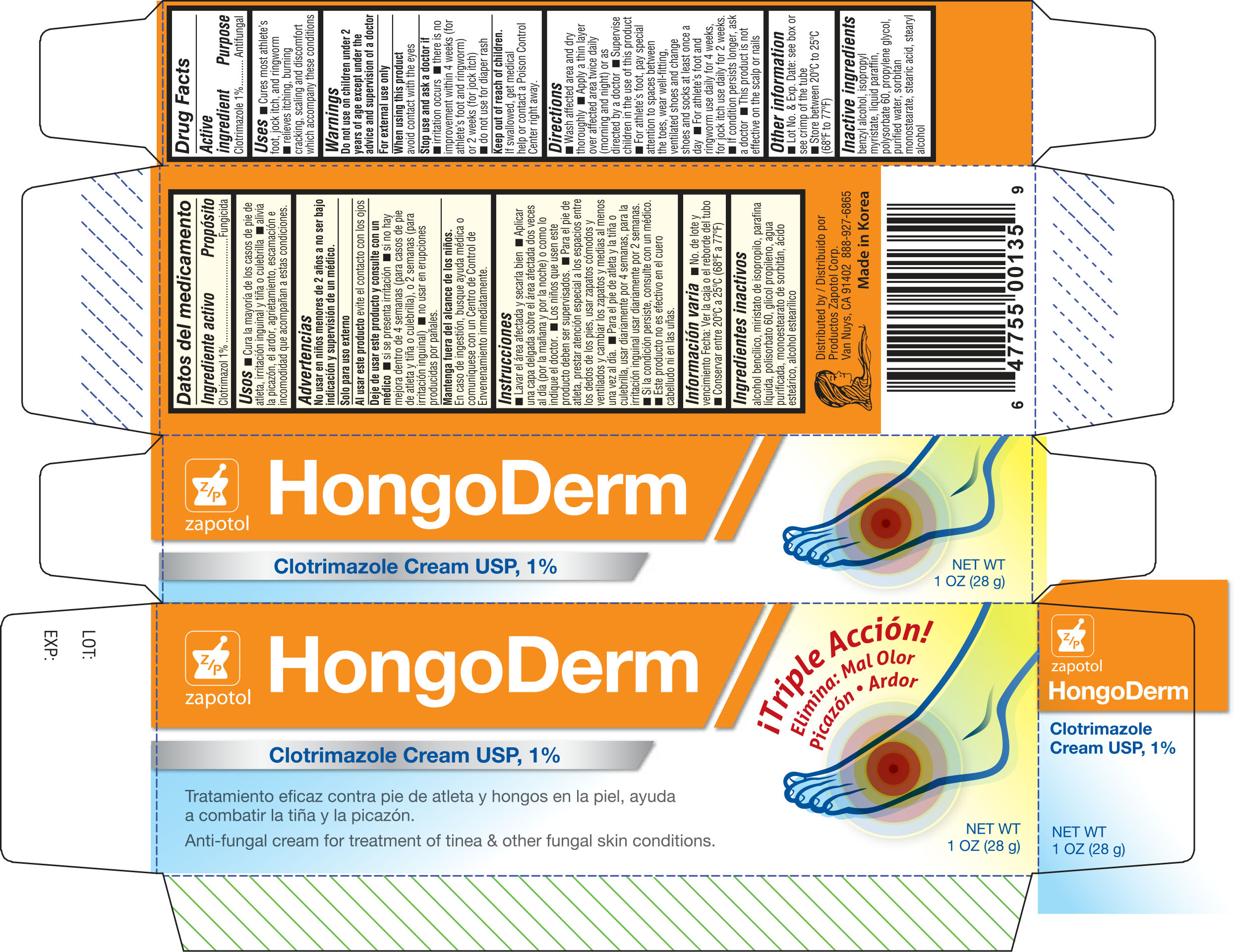 DRUG LABEL: Zapotol Clotrimazole
NDC: 59428-359 | Form: CREAM
Manufacturer: Zapotol Corp.
Category: otc | Type: HUMAN OTC DRUG LABEL
Date: 20161013

ACTIVE INGREDIENTS: CLOTRIMAZOLE 10 mg/100 g
INACTIVE INGREDIENTS: BENZYL ALCOHOL; ISOPROPYL MYRISTATE; PARAFFIN; POLYSORBATE 60; PROPYLENE GLYCOL; WATER; SORBITAN MONOSTEARATE; STEARIC ACID; STEARYL ALCOHOL

Active ingredient Purpose

Clotrimazole 1%--------------------------------------------- Antifungal

Uses

- Cures most athlete's foot, jock itch, and ringworm
- relieves itching, burning, cracking, scaling and discomfort which accompany these conditions

Warnings

Do not use on children under 2 years of age except under the advice and supervision of a doctor

For external use only

When using this product avoid contact with the eyes

Stop use and ask a doctor if

- irritation occurs
- there is no improvement within 4 weeks (for athlete's foot and ringworm) or 2 weeks (for jock itch)
- do not use for diaper rash

Keep out of reach of childern

If swallowed, get medical help or contact a Poison Control Center right away.

INDICATIONS AND USAGE

Direction

- Wash affected area and dry thoroughly
- Apply a thin layer over affected area twice daily (morning and night) or as directed by a doctor
- Supervise children in the use of this product
- For athlete's foot, pay special attention to spaces between the toes, wear well fitting ventilated shoes and change shoes and socks at least once a day
- For athlete's foot and ringworm use daily for 4 weeks, for jock itch use daily for 2 weeks
- If condition persists longer, ask a doctor
- This product is not effective on the scalp or nails

Other information

Lot No. & Exp. Date;see box or see crimp of the tube

Store between 20°C to 25°C (68°F to 77°F)

Inactive ingredients

benzyl alcohol, isopropyl myristate, liquid paraffin, polysorbate 60, propylene glycol, purified water, sorbitan monostearate, stearic acid, stearyl alcohol

DOSAGE AND ADMINISTRATION

DISTRIBUTED BY:

PRODUCTOS ZAPOTOL CORP.

Van Nuys, CA 91402

888-927-6865

Made in Korea